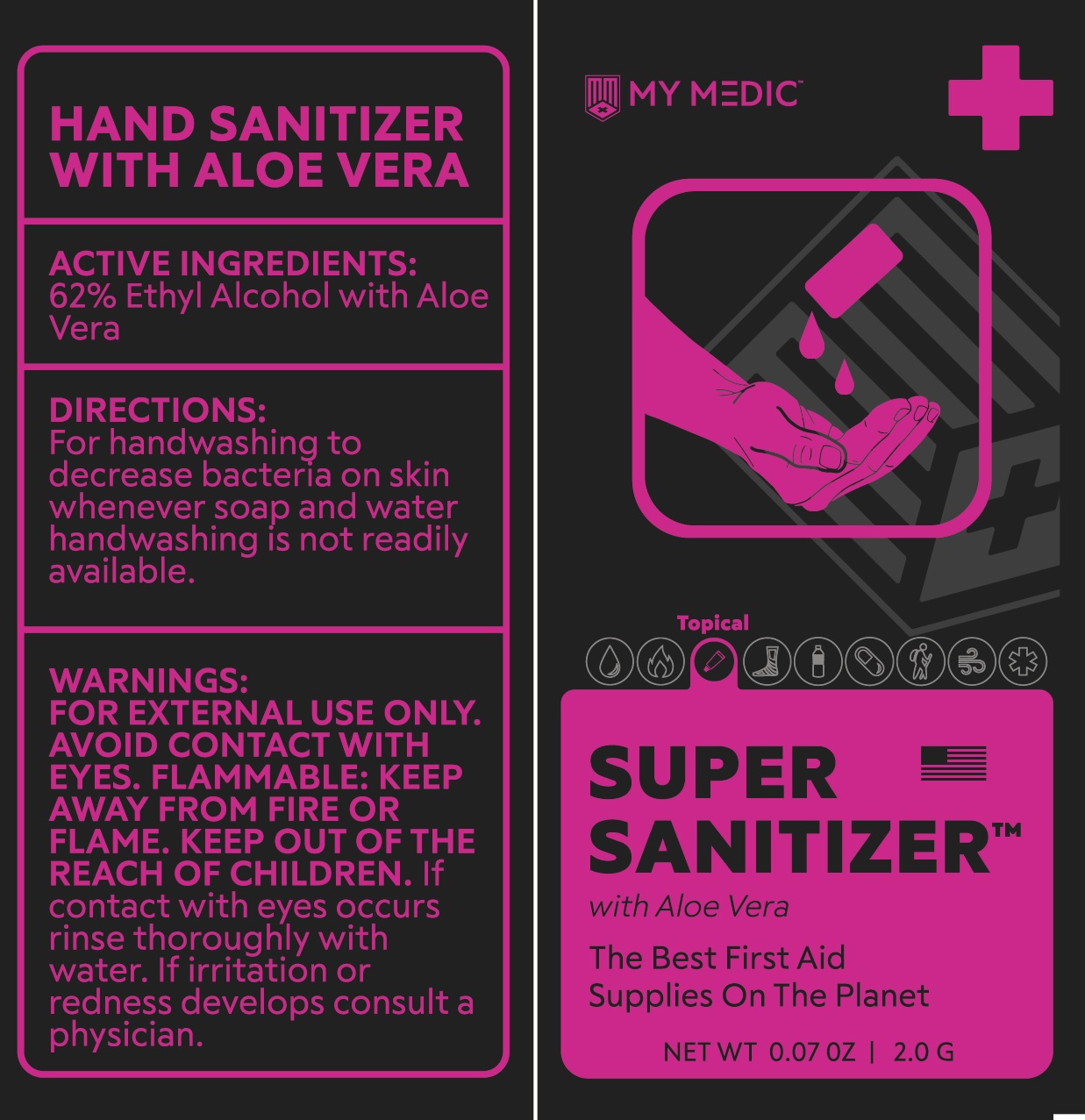 DRUG LABEL: my medic super Sanitizer with aloe vera
NDC: 71734-308 | Form: GEL
Manufacturer: JIANGMEN SHUIZIRUN SANITARY ARTICLES CO., LTD.
Category: otc | Type: HUMAN OTC DRUG LABEL
Date: 20200331

ACTIVE INGREDIENTS: ALCOHOL 62 mL/100 mL
INACTIVE INGREDIENTS: WATER; GLYCERIN; TROLAMINe; CARBOMER 934

Active ingredient

62% Ethyl Alcohol with aloe vera

Purpose

Antiseptic

Use

For handwashing to decrease bacteria on skin whenever soap and water handwashing is not readily available.

Warnings

For external use only.

For external use only.

Avoid contact with eyes.

Flammable: keep away from fire or flame.

If contact with eyes occurs, rinse thoroughly with water, if irritation or redness develops consult a physician.

Keep out of reach of children.

If swallowed, get medical help or contact a Poison Control Center right away.

Directions

- Place enough to cover both hands in the palm, and rub hands together until dry
- Children under 6 years of age should be supervised bu an adult when appling this products.

Inactive ingredients

Water, Glycerin, Carbomer, Triethanolamine, Disodium EDTA

other information

- Do not store above 105 Fahrenheit.
- May discolor certain fabrics or surfaces.
- Harmful to wood finishes and plastics.